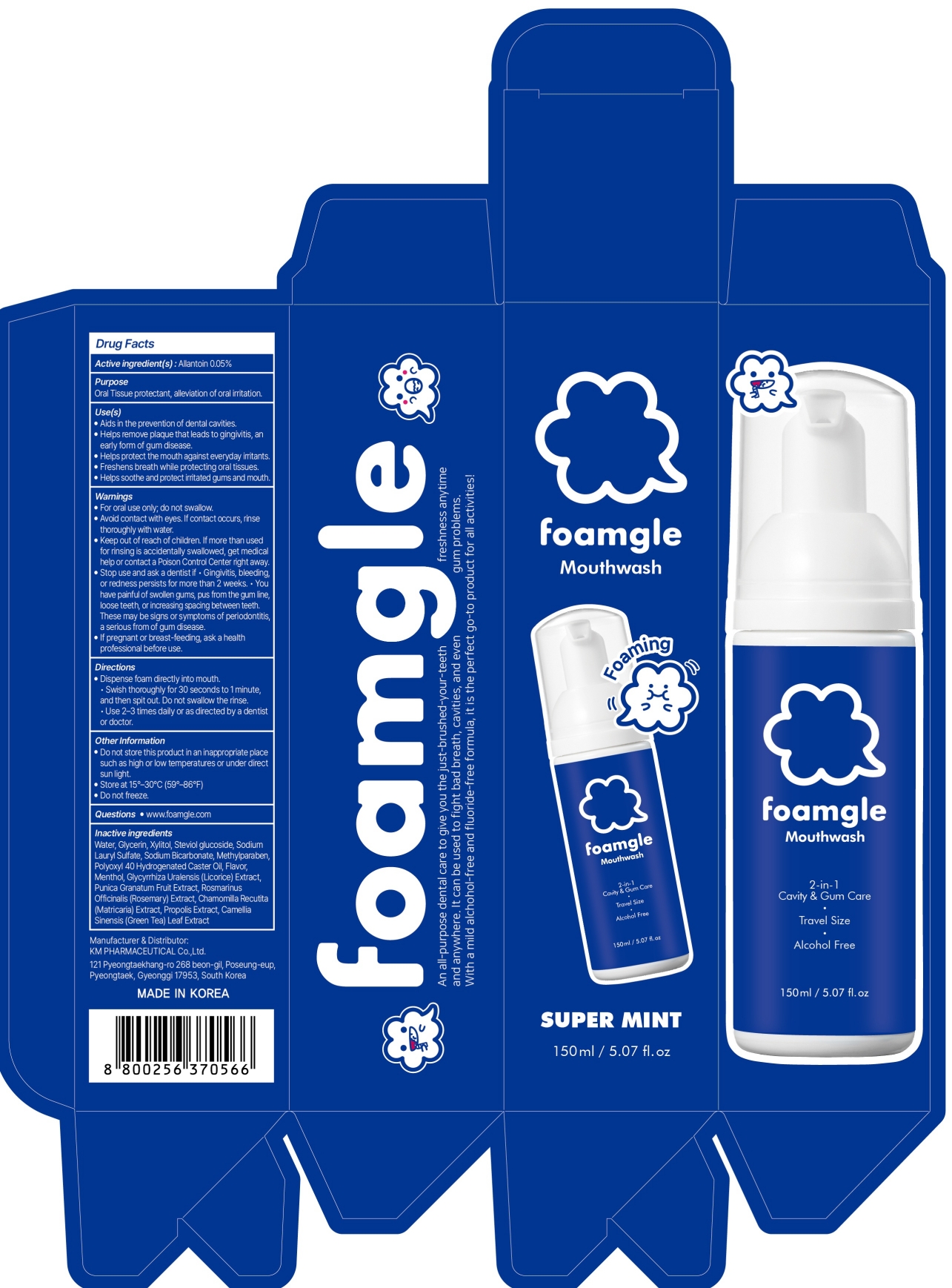 DRUG LABEL: Foamgle Foam Super Mint
NDC: 50555-220 | Form: MOUTHWASH
Manufacturer: KMPHARMACEUTICAL CO.,LTD
Category: otc | Type: HUMAN OTC DRUG LABEL
Date: 20260301

ACTIVE INGREDIENTS: ALLANTOIN 0.05 g/100 mL
INACTIVE INGREDIENTS: CHAMOMILE; PROPOLIS WAX; ROSEMARY; POMEGRANATE; PEG-40 HYDROGENATED CASTOR OIL; SODIUM BICARBONATE; XYLITOL; METHYLPARABEN; GLYCERIN; SODIUM LAURYL SULFATE; WATER; MENTHOL

Foamgle Foam Mouthwash – Super Mint 150mL

Active ingredient(s)

Allantoin 0.05%

Purpose

Oral Tissue protectant, alleviation of oral irritation

INDICATIONS AND USAGE

Use(s)

■ Aids in the prevention of dental cavities.

■ Helps remove plaque that leads to gingivitis, an early form of gum disease.

■ Helps protect the mouth against everyday irritants

■ Freshens breath while protecting oral tissues

■ Helps soothe and protect irritated gums and mouth

Warnings

■ For oral use only; do not swallow.
■ Avoid contact with eyes. If contact occurs, rinse thoroughly with water.

■ Keep out of reach of children. If more than used for rinsing is accidentally swallowed, get medical help or contact a Poison Control Center right away.

■ Stop use and ask a dentist if • Gingivitis, bleeding, or redness persists for more than 2 weeks. • You have painful of swollen gums, pus from the gum line, loose teeth, or increasing spacing between teeth. These may be signs or symptoms of periodontitis, a serious from of gum disease.

■ If pregnant or breast-feeding, ask a health professional before use.

Directions

■ Dispense foam directly into mouth • Swish thoroughly for 30 seconds to 1 minute, and then spit out. Do not swallow the rinse • Use 2–3 times daily or as directed by a dentist or doctor.

Other Information

■ Do not store this product in an inappropriate place such as high or low temperatures or under direct sun light

■ Store at 15°–30°C (59°–86°F)

■ Do not freeze.

Questions

■ www.foamgle.com

Inactive ingredients

Water, Glycerin, Xylitol, Steviol glucoside, Sodium Lauryl Sulfate, Sodium Bicarbonate, Methylparaben, Polyoxyl 40 Hydrogenated Caster Oil, Flavor, Menthol, Glycyrrhiza Uralensis (Licorice) Extract, Punica Granatum Fruit Extract, Rosmarinus Officinalis (Rosemary) Extract, Chamomilla Recutita (Matricaria) Extract, Propolis Extract, Camellia Sinensis (Green Tea) Leaf Extract